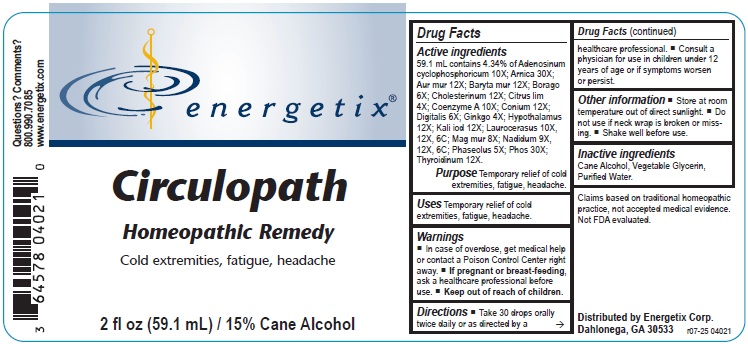 DRUG LABEL: Circulopath
NDC: 64578-0146 | Form: LIQUID
Manufacturer: Energetix Corporation
Category: homeopathic | Type: HUMAN OTC DRUG LABEL
Date: 20251217

ACTIVE INGREDIENTS: ADENOSINE CYCLIC PHOSPHATE 10 [hp_X]/59.1 mL; ARNICA MONTANA 30 [hp_X]/59.1 mL; GOLD TRICHLORIDE 12 [hp_X]/59.1 mL; BARIUM CHLORIDE DIHYDRATE 12 [hp_X]/59.1 mL; BORAGE 6 [hp_X]/59.1 mL; CHOLESTEROL 12 [hp_X]/59.1 mL; LEMON JUICE 4 [hp_X]/59.1 mL; COENZYME A 10 [hp_X]/59.1 mL; CONIUM MACULATUM FLOWERING TOP 12 [hp_X]/59.1 mL; DIGITALIS 6 [hp_X]/59.1 mL; GINKGO 4 [hp_X]/59.1 mL; BOS TAURUS HYPOTHALAMUS 12 [hp_X]/59.1 mL; POTASSIUM IODIDE 12 [hp_X]/59.1 mL; PRUNUS LAUROCERASUS LEAF 10 [hp_X]/59.1 mL; MAGNESIUM CHLORIDE 8 [hp_X]/59.1 mL; NADIDE 9 [hp_X]/59.1 mL; KIDNEY BEAN 5 [hp_X]/59.1 mL; PHOSPHORUS 30 [hp_X]/59.1 mL; THYROID, BOVINE 12 [hp_X]/59.1 mL
INACTIVE INGREDIENTS: WATER; GLYCERIN; ALCOHOL

Circulopath

Active ingredients

59.1 mL contains 4.34% of Adenosinum cyclophosphoricum 10X; Arnica 30X; Aur mur 12X; Baryta mur12X; Borago 6X; Cholesterinum 12X; Citrus lim 4X; Coenzyme A 10X; Conium 12X; Digitalis 6X; Ginkgo 4X; Hypothalamus 12X; Kali iod 12X; Laurocerasus 10X, 12X, 6C; Mag mur 8X, Nadidum 9X, 12X, 6C; Phaseolus 5X; Phos 30X; Thyroidinum 12X

Claims based on traditional homeopathic practice, not accepted medical evidence. Not FDA evaluated.

Uses

Temporary relief of cold extremities, fatigue, headache.

Warnings

- In case of overdose, get medical help or contact a Poison Control Center right away.
- If pregnant or breast-feeding, ask a health professional before use.

• Keep out of reach of children.

Directions

- Take 30 drops orally twice daily or as directed by a healthcare professional.
- Consult a physician for use in children under 12 years of age or if symptoms worsen or persist.

Other information

- Store at room temperature out of direct sunlight.
- Do not use if neck wrap is broken or missing.
- Shake well before use.

Inactive Ingredients

Cane Alcohol, Glycerin, Purified Water.

QUESTIONS

Distributed by Energetix Corp.

Dahlonega, GA 30533

Questions? Comments?

800.990.7085

www.energetix.com

PACKAGE LABEL

energetix

Circulopath

Homeopathic Remedy

Cold extremities, fatigue, headache

2 fl oz (59.1 mL) / 15% Cane Alcohol

Purpose Temporary relief of cold extremeties, fatigue, headache.